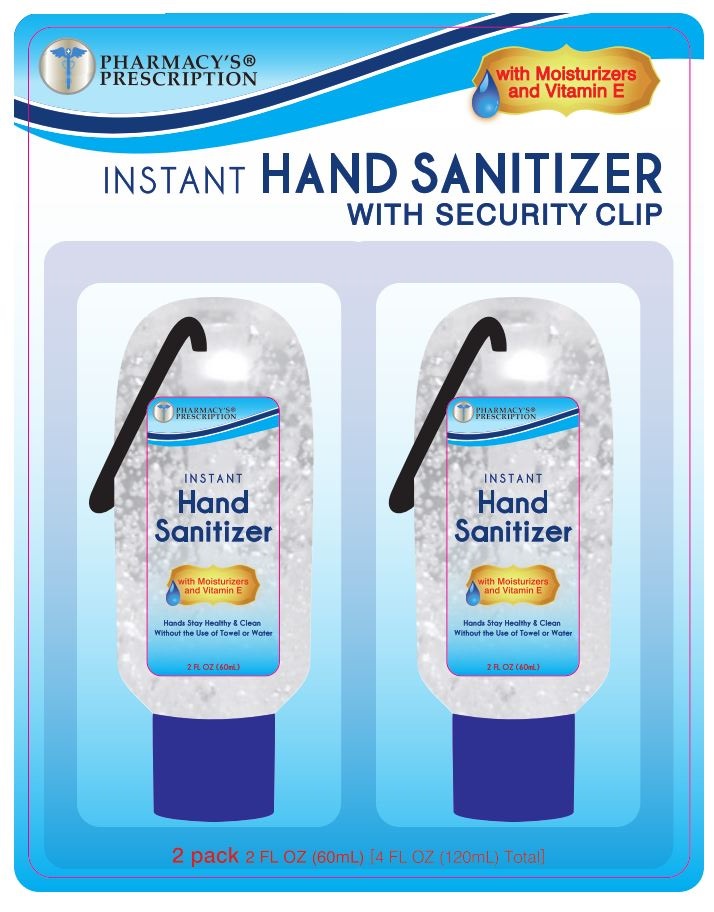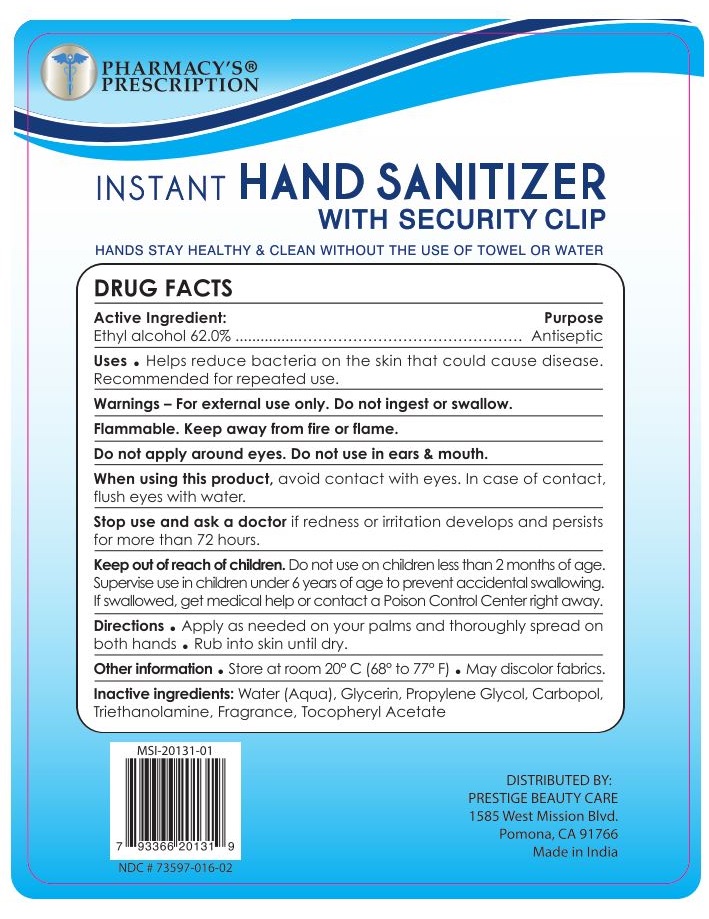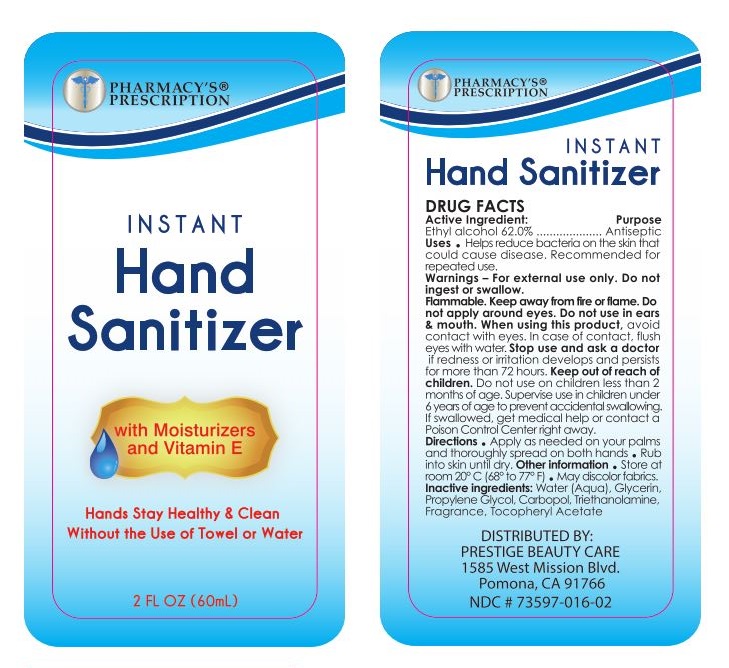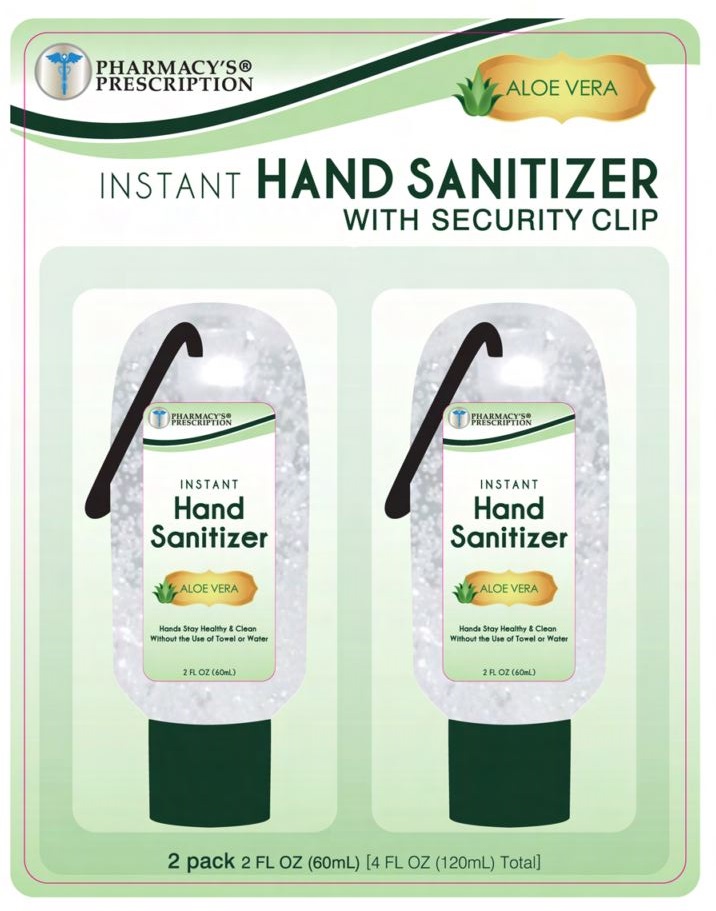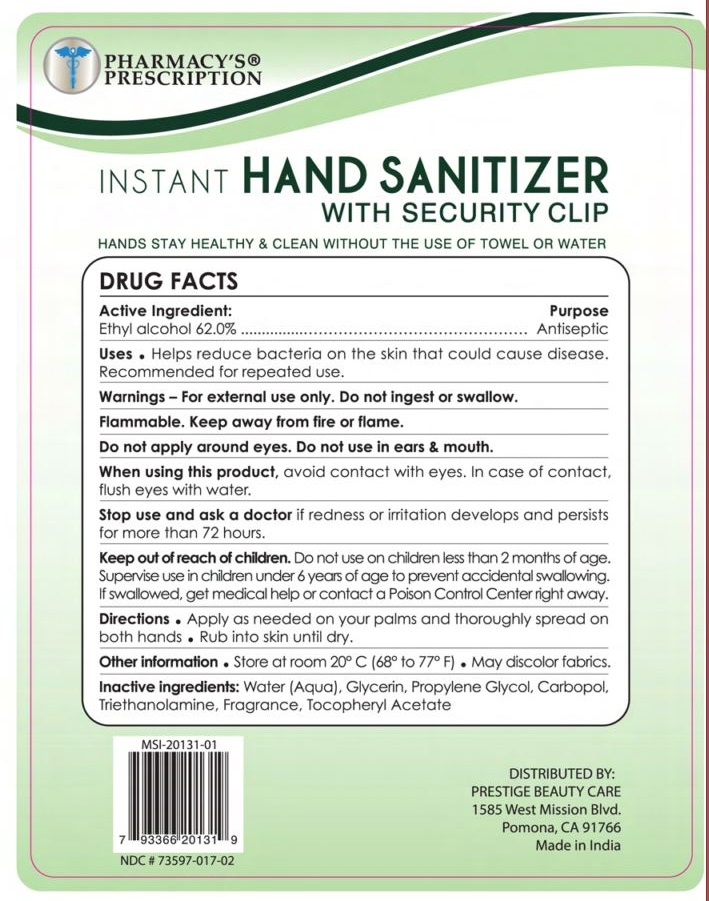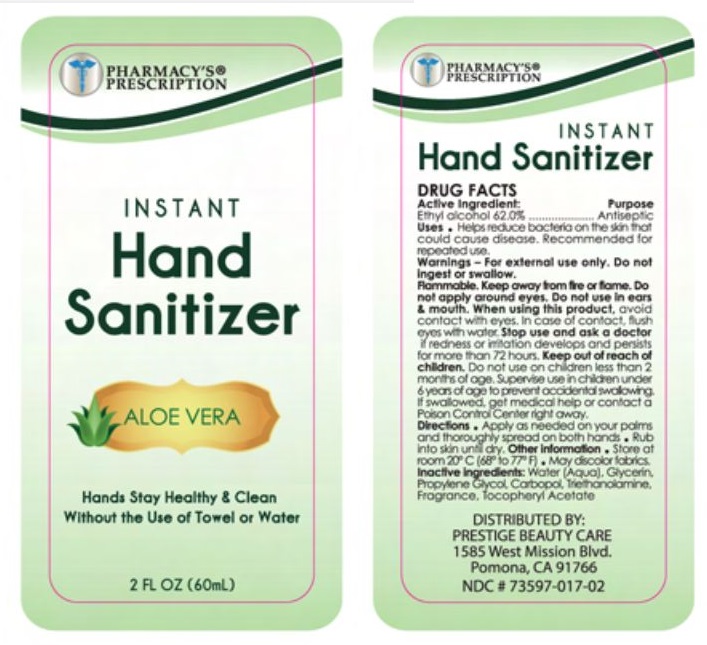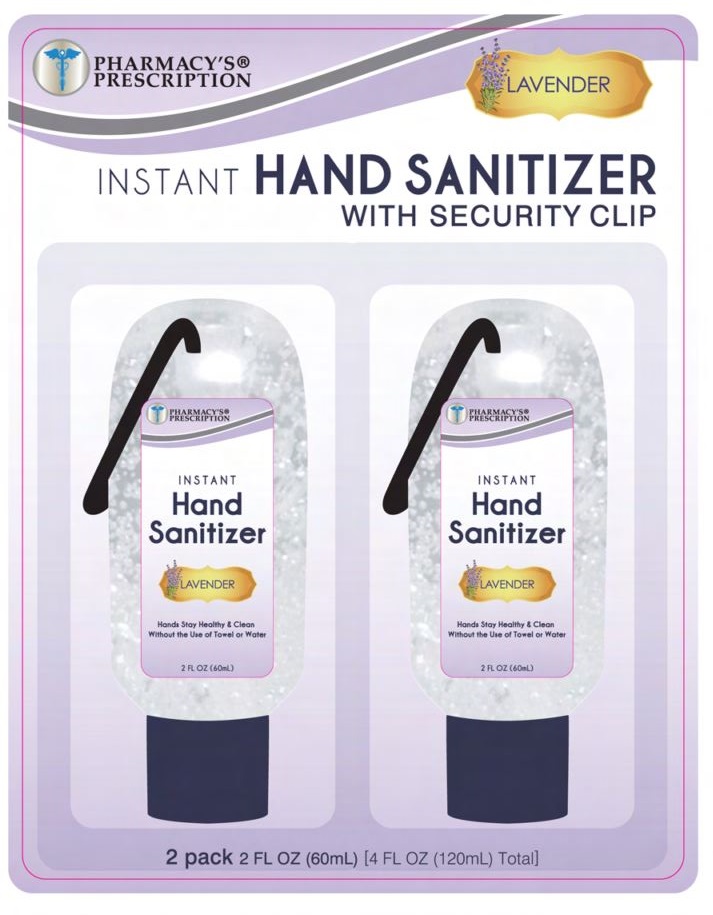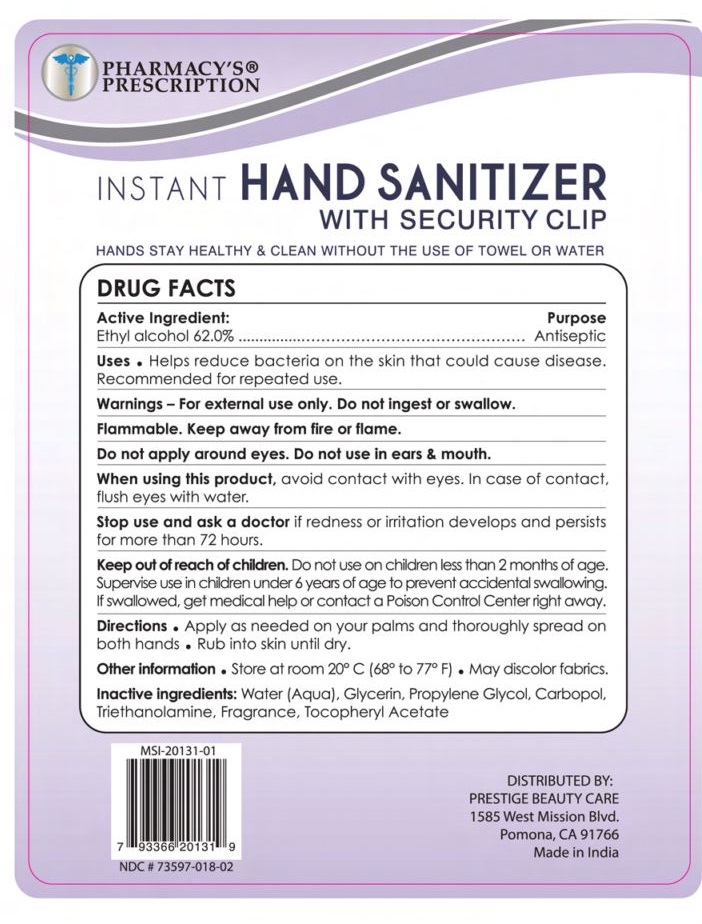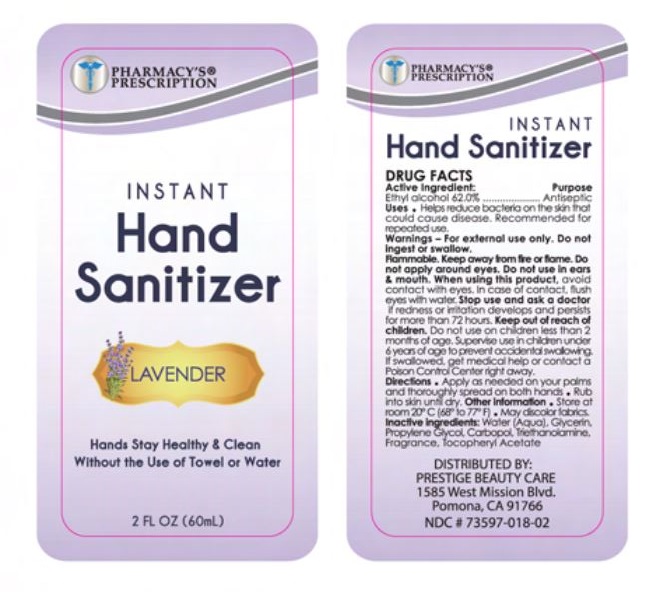 DRUG LABEL: Pharmacys Prescription Hand Sanitizer Aloe
NDC: 73597-017 | Form: GEL
Manufacturer: Mission Series Inc. dba Prestige Beauty Care
Category: otc | Type: HUMAN OTC DRUG LABEL
Date: 20220315

ACTIVE INGREDIENTS: ALCOHOL 62 mL/100 mL
INACTIVE INGREDIENTS: WATER; GLYCERIN; PROPYLENE GLYCOL; CARBOMER HOMOPOLYMER, UNSPECIFIED TYPE; .ALPHA.-TOCOPHEROL ACETATE; TROLAMINE

Pharmacys Prescription Hand Sanitizer

Active Ingredient

Active Ingredient: Ethyl Alcohol 62%

Purpose

Purpose: Antiseptic

Uses - Helps reduce bacteria on the skin that could cause disease. Recommended for repeated use.

Warnings

Warnings - For external use only. Do not ingest or swallow.

Flammable. Keep away from fire or flame.

Do not apply around eyes. Do not use in ears & mouth.

Indications & Usage Section

When using this product, avoid contact with eyes. In case of contact, flush eyes with water.

Stop Use

Stop use and ask a doctor if redness or irritation develops and persists for more than 72 hours.

Keep out of reach of children. Do not use on children less than 2 months of age.

Supervise use in children under 6 years of age to prevent accidental swallowing.

If swallowed, get medical help or contact a Poison Control Center right away.

Directions

Directions ● apply as needed on your palms and thoroughly spread on both hands ● rub into skin until dry.

Other Information

Other Information ● store at 20° C (68° to 77° F) ● may discolor fabrics.

Inactive Ingredients

Inactive Ingredients: Water (Aqua), Glycerin, Propylene Glycol, Carbopol, Triethanolamine, Tocopheryl Acetate